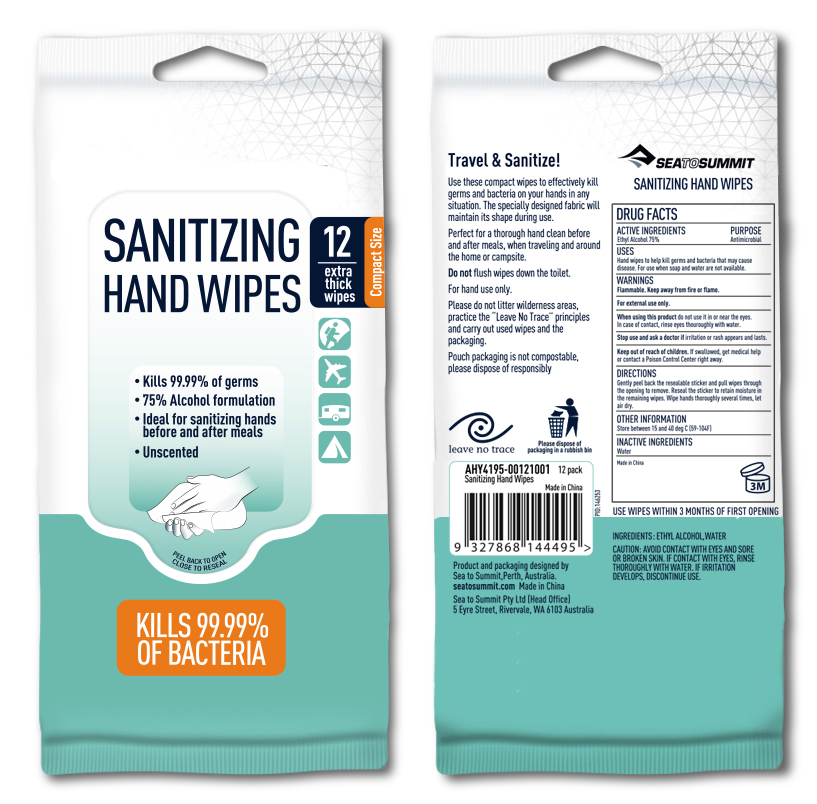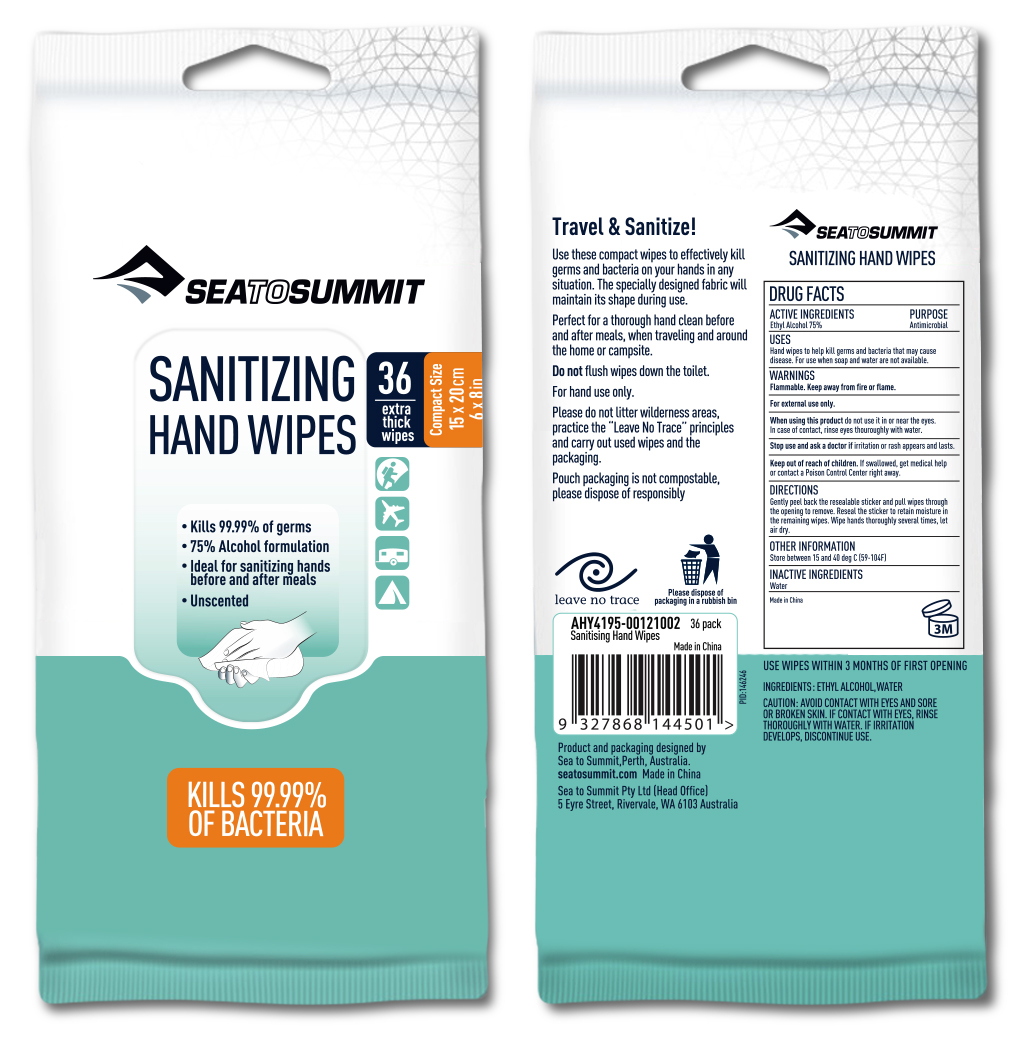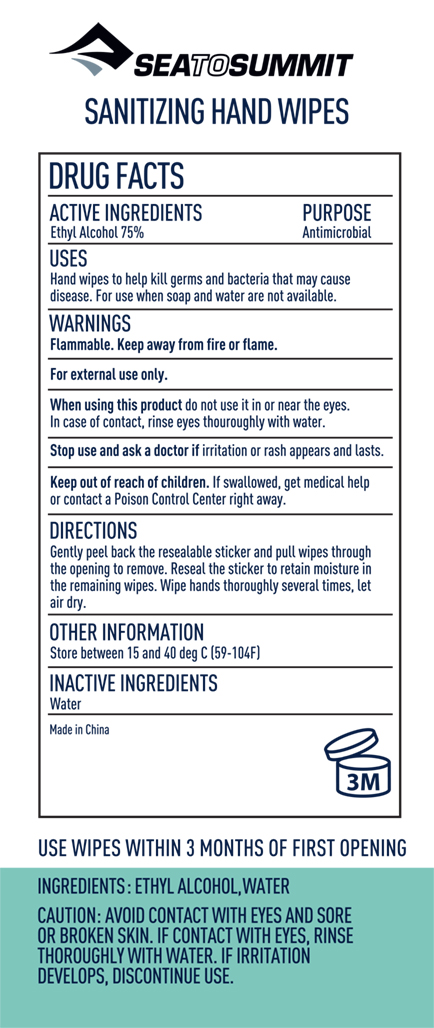 DRUG LABEL: Wet Wipe 12 Pack
NDC: 79238-1120 | Form: SWAB
Manufacturer: Sea to Summit Pty Ltd
Category: otc | Type: HUMAN OTC DRUG LABEL
Date: 20211115

ACTIVE INGREDIENTS: ALCOHOL 75 mL/100 mL
INACTIVE INGREDIENTS: WATER 25 mL/100 mL

Wet Wipe 75% Alcohol; 12 Count, 36 Count